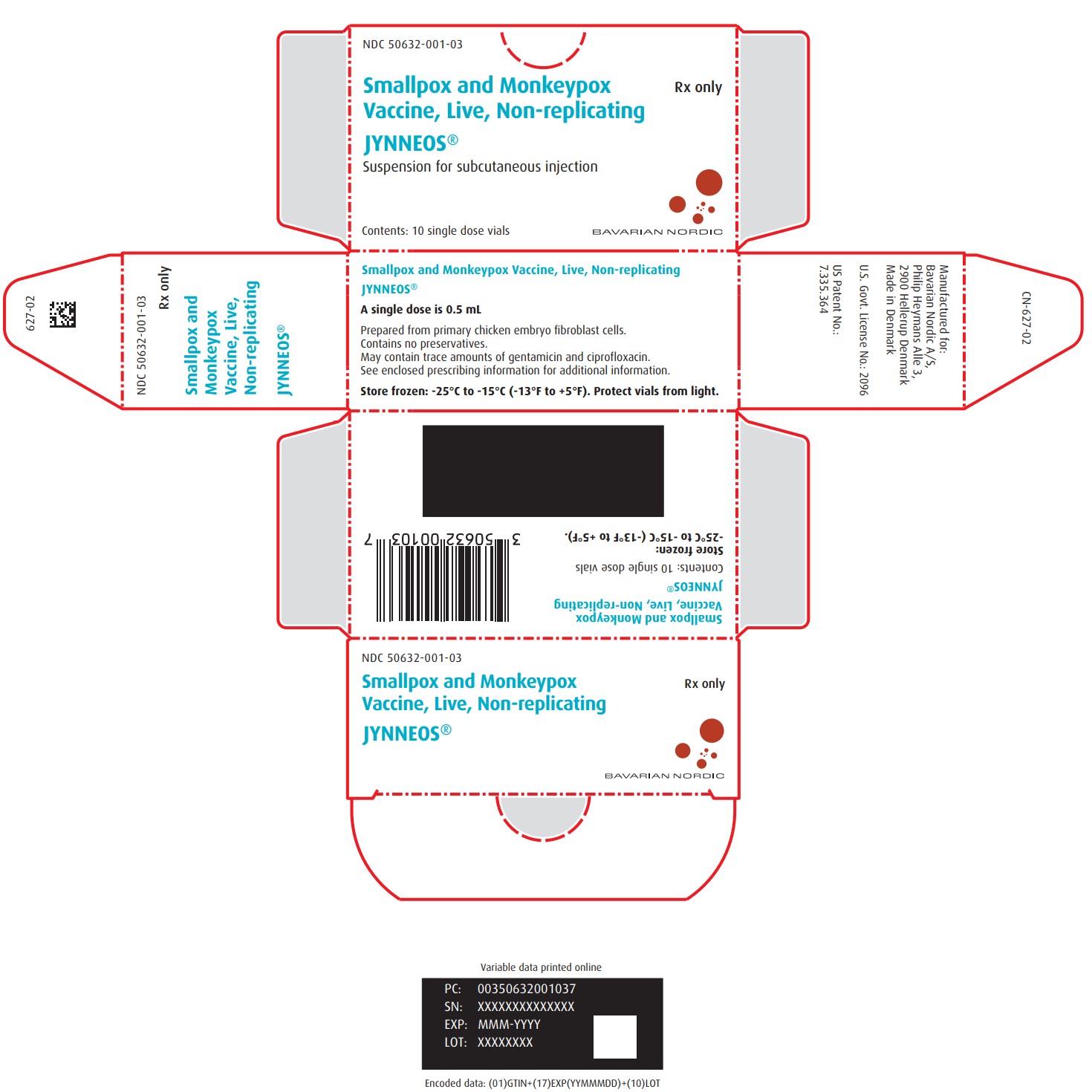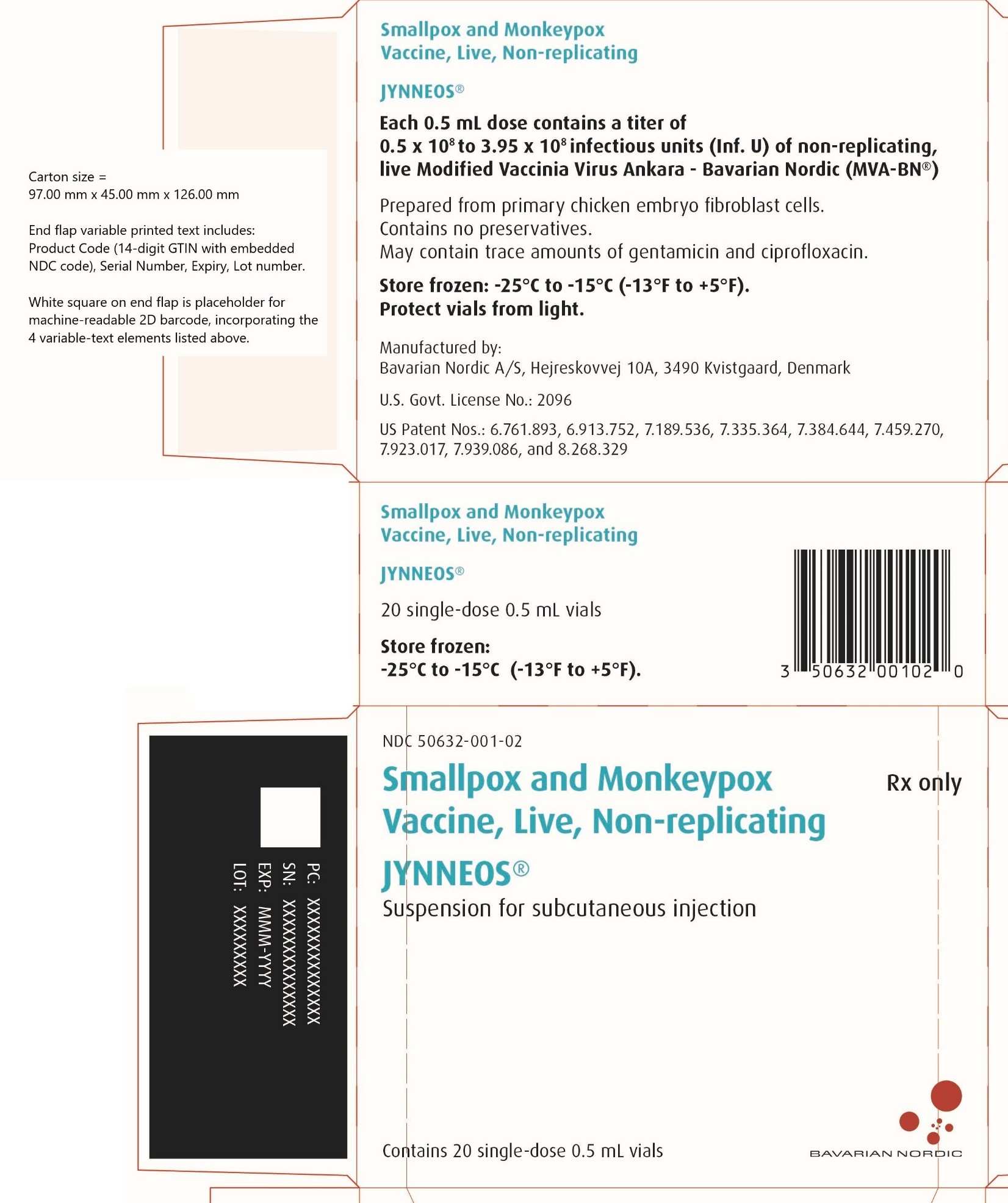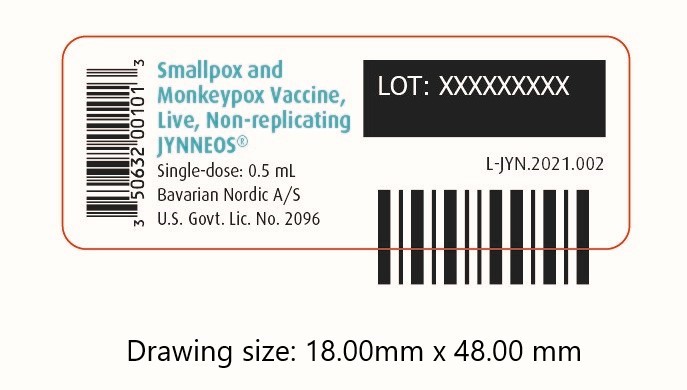 DRUG LABEL: JYNNEOS
NDC: 50632-001 | Form: INJECTION, SUSPENSION
Manufacturer: Bavarian Nordic A/S
Category: other | Type: VACCINE LABEL
Date: 20231115

ACTIVE INGREDIENTS: VACCINIA VIRUS MODIFIED STRAIN ANKARA-BAVARIAN NORDIC NON-REPLICATING ANTIGEN 50000000 1/0.5 mL
INACTIVE INGREDIENTS: TROMETHAMINE; SODIUM CHLORIDE; WATER

HIGHLIGHTS OF PRESCRIBING INFORMATION

These highlights do not include all the information needed to use JYNNEOS safely and effectively. See full prescribing information for JYNNEOS.
JYNNEOS (Smallpox and Monkeypox Vaccine, Live, Non-replicating) suspension for subcutaneous injection
Initial U.S. Approval: 2019

RECENT MAJOR CHANGES

Dosage and Administration (2.2) 03/2023
Warnings and Precautions (5.2) 09/2023

1 INDICATIONS AND USAGE

JYNNEOS is a vaccine indicated for prevention of smallpox and monkeypox disease in adults 18 years of age and older determined to be at high risk for smallpox or monkeypox infection. (1)

2 DOSAGE AND ADMINISTRATION

For subcutaneous injection only.

Administer two doses (0.5 mL each) 4 weeks apart. (2.1, 2.2)

3 DOSAGE FORMS AND STRENGTHS

Suspension for injection. Each dose (0.5 mL) is supplied in a single-dose vial. (3)

6 ADVERSE REACTIONS

- In smallpox vaccine-naïve healthy adults, the most common (> 10%) solicited injection site reactions were pain (84.9%), redness (60.8%), swelling (51.6%), induration (45.4%), and itching (43.1%); the most common solicited systemic adverse reactions were muscle pain (42.8%), headache (34.8%), fatigue (30.4%), nausea (17.3%) and chills (10.4%). (6.1)
- In healthy adults previously vaccinated with a smallpox vaccine, the most common (> 10%) solicited injection site reactions were redness (80.9%), pain (79.5%), induration (70.4%), swelling (67.2%), and itching (32.0%); the most common solicited systemic adverse reactions were fatigue (33.5%), headache (27.6%), and muscle pain (21.5%). (6.1)
- The frequencies of solicited local and systemic adverse reactions among adults with HIV-infection and adults with atopic dermatitis were generally similar to those observed in healthy adults. (6.1)

To report SUSPECTED ADVERSE REACTIONS, contact Bavarian Nordic at toll-free phone 1-800-675-9596 or VAERS at 1-800-822-7967 or www.vaers.hhs.gov.

FULL PRESCRIBING INFORMATION

1 INDICATIONS AND USAGE

JYNNEOS is a vaccine indicated for prevention of smallpox and monkeypox disease in adults 18 years of age and older determined to be at high risk for smallpox or monkeypox infection.

2 DOSAGE AND ADMINISTRATION

For subcutaneous injection only.

2.1 Dose and Schedule

Administer two doses (0.5 mL each) of JYNNEOS 4 weeks apart.

2.2 Preparation and Administration

Allow the vaccine to thaw and reach room temperature before use. Once thawed, the vaccine may be kept at +2°C to +8°C (+36°F to +46°F) for 4 weeks. Do not refreeze.

When thawed, JYNNEOS is a milky, light yellow to pale white colored suspension.
Parenteral drug products should be inspected visually for particulate matter and discoloration prior to administration, whenever solution and container permit. If either of these conditions exists, the vaccine should not be administered.

Swirl the vial gently before use for at least 30 seconds. Withdraw a dose of 0.5 mL into a sterile syringe for injection.

Administer JYNNEOS by subcutaneous injection, preferably into the upper arm.

3 DOSAGE FORMS AND STRENGTHS

JYNNEOS is a suspension for injection. Each dose (0.5 mL) is supplied in a single‑dose vial.

5 WARNINGS AND PRECAUTIONS

5.1 Severe Allergic Reactions

Appropriate medical treatment must be available to manage possible anaphylactic reactions following administration of JYNNEOS.

Persons who experienced a severe allergic reaction following a previous dose of JYNNEOS or following exposure to any component of JYNNEOS may be at increased risk for severe allergic reactions after JYNNEOS. The risk for a severe allergic reaction should be weighed against the risk for disease due to smallpox or monkeypox.

5.2 Syncope

Syncope (fainting) has been reported following vaccination with JYNNEOS. Procedures should be in place to avoid injury from fainting.

5.3 Altered Immunocompetence

Immunocompromised persons, including those receiving immunosuppressive therapy, may have a diminished immune response to JYNNEOS.

5.4 Limitations of Vaccine Effectiveness

Vaccination with JYNNEOS may not protect all recipients.

6 ADVERSE REACTIONS

6.1 Clinical Trials Experience

Because clinical trials are conducted under widely varying conditions, adverse reaction rates observed in the clinical trials of a vaccine cannot be directly compared with rates in the clinical trials of another vaccine, and may not reflect the rates observed in practice. There is the possibility that broad use of JYNNEOS could reveal adverse reactions not observed in clinical trials.

The overall clinical trial program included 22 studies and a total of 7,859 individuals 18 through 80 years of age who received at least 1 dose of JYNNEOS (7,093 smallpox vaccine-naïve and 766 smallpox vaccine-experienced individuals).

Solicited Adverse Reactions

Solicited Adverse Reactions in Smallpox Vaccine-Naïve Individuals:

The safety of JYNNEOS in smallpox vaccine-naïve individuals was evaluated in Study 1 [1], a randomized, double-blind, placebo-controlled study conducted in the US in which vaccinia-naïve adults ages 18 to 40 years received either two doses of JYNNEOS (N=3003), or two injections of Tris-Buffered Saline (placebo, N=1002) four weeks apart.

In the total study population, the mean age was 28 years; 47.9% of the subjects were men; 77.4% were white/Caucasian, 17.8% black/African American, 1.9% Asian, 0.5% American Indian/Alaska Native, 0.4% Native Hawaiian/Other Pacific, 1.9% other racial groups; and 11.4% of subjects were of Hispanic/Latino ethnicity. The demographic compositions of JYNNEOS and placebo groups were similar.

In Study 1, subjects were monitored for local and systemic adverse reactions using diary cards for an 8-day period starting on the day of each vaccination. The frequencies of solicited local and systemic adverse reactions following any dose of JYNNEOS are presented in Table 1.

Table 1: Percentages of Subjects with Solicited Local Injection Site Reactions and Systemic Adverse Reactions within 8 Days of Administration of Any Dose of JYNNEOS in Adults 18 to 40 Years of Age, Study 1x
Reaction | JYNNEOS N =2943 % | Placebo N = 980 %
Local (Injection site) | -- | --
Pain | 84.9 | 19.1
Pain, Grade 3a | 7.4 | 1.0
Redness | 60.8 | 17.7
Redness ≥ 100 mm | 1.5 | 0.0
Swelling | 51.6 | 5.6
Swelling ≥ 100 mm | 0.8 | 0.0
Induration | 45.4 | 4.6
Induration ≥ 100 mm | 0.3 | 0.0
Itching | 43.1 | 11.7
Itching, Grade 3b | 1.6 | 0.2
Systemic | -- | --
Muscle Pain | 42.8 | 17.6
Muscle Pain, Grade 3b | 2.6 | 0.7
Headache | 34.8 | 25.6
Headache, Grade 3b | 2.4 | 2.1
Fatigue | 30.4 | 20.5
Fatigue, Grade 3b | 3.0 | 1.3
Nausea | 17.3 | 13.1
Nausea, Grade 3b | 1.5 | 1.2
Chills | 10.4 | 5.8
Chills, Grade 3b | 1.0 | 0.3
Feverc | 1.7 | 0.9
Fever, Grade ≥3c | 0.2 | 0.0
x NCT01144637
a Grade 3 pain defined as spontaneously painful
b Grade 3 itching, muscle pain, headache, fatigue, nausea and chills defined as preventing routine daily activities
c Fever defined as oral temperature ≥ 100.4°F (≥ 38°C), Grade ≥ 3 fever defined as ≥ 102.2°F (≥ 39.0°C)
N=number of subjects

In Study 1, the majority of solicited local and systemic adverse reactions reported with JYNNEOS had a median duration of 1 to 6 days. In general, there were similar proportions of subjects reporting solicited local or systemic reactions of any severity after Dose 2 of JYNNEOS compared with Dose 1, with the exception of injection site pain, which was more commonly reported following Dose 1 (79.3%) than Dose 2 (69.9%).

Solicited Adverse Reactions in Persons Previously Vaccinated with a Smallpox Vaccine:

Three studies (Study 2, Study 3, and Study 4, [2-4]) conducted in the US and Germany evaluated the safety of JYNNEOS in 409 persons previously vaccinated with a smallpox vaccine who received one or two doses of JYNNEOS (mean age 39 years, range 20-80 years; 59% women; 98.8% white/Caucasian; 0.7% Asian; 0.5% black/African American). Subjects were monitored for local and systemic adverse reactions using diary cards for an 8-day period starting on the day of each vaccination. Across all three studies, solicited local adverse reactions reported following any dose of JYNNEOS were redness (80.9%), pain (79.5%), induration (70.4%), swelling (67.2%), and itching (32.0%) at the injection site; solicited systemic adverse reactions reported following any dose of JYNNEOS were fatigue (33.5%), headache (27.6%), muscle pain (21.5%), nausea (9.8%), chills (0.7%), and fever (0.5%).

Solicited Adverse Reactions in HIV-infected Individuals:

The safety of JYNNEOS in HIV-infected individuals was evaluated in Study 5 [5], an open label trial conducted in the US that included 351 HIV-infected smallpox vaccine-naïve subjects, 131 HIV-infected subjects who previously received smallpox vaccine, 88 non-HIV-infected smallpox vaccine-naïve subjects and 9 non-HIV-infected subjects who had previously received a smallpox vaccine. The racial/ethnic and gender compositions of HIV-infected smallpox vaccine-naïve subjects and those who had previously received smallpox vaccine were similar and overall were 17.0% women; 45.8% white/Caucasian; 0.4% Asian; 33.2% black/African American; 19.0% Hispanic/Latino ethnicity; the HIV-infected smallpox vaccine-naïve group tended to be younger (mean age 37 years) compared to those who had previously received a smallpox vaccine (mean age 45 years). Subjects had CD4 counts ≥ 200 and ≤ 750 cells/µL at study entry.

Solicited local and systemic adverse reactions were reported at similar or lower frequencies in HIV-infected smallpox vaccine-naïve subjects as compared to those seen in non-HIV-infected smallpox vaccine-naïve individuals in this study.

In HIV-infected subjects with previous smallpox vaccine exposure, fever and chills were reported in 1.5% and 8.4% of subjects respectively. Frequencies of other solicited local and general adverse reactions in this population were similar to those reported in Studies 2-4 in non-HIV-infected subjects who had previously received smallpox vaccination.

Solicited Adverse Reactions in Individuals with Atopic Dermatitis:

The safety of JYNNEOS in smallpox vaccine-naïve subjects with currently active or a history of atopic dermatitis (AD) was evaluated in a multicenter, open-label clinical study (Study 6 [6]) conducted in the US and Mexico that included 350 subjects with AD and 282 subjects without AD. In the overall study the mean age of subjects was 27 years (range 18-42 years), and subjects were 59.0% women, 39.4% white/Caucasian, 10.9% Asian, 9.0% black/African American, 2.2% Other, and 38.4% Hispanic/Latino ethnicity. Demographic compositions were similar between subjects with and without AD. In subjects with AD, solicited local and systemic adverse reactions were reported at similar frequencies as those in subjects without AD in this study, with the exception of redness (61.2% with AD vs. 49.3% without AD), swelling (52.2% with AD vs. 40.8% without AD), chills (15.9% with AD vs. 7.8% without AD) and headache (47.2% with AD vs. 34.8% without AD).

Serious Adverse Events

The integrated analyses of serious adverse events (SAEs) pooled safety data across 22 studies, which included a total of 7,093 smallpox vaccine-naïve subjects and 766 smallpox vaccine-experienced subjects who received at least 1 dose of JYNNEOS and 1,206 smallpox vaccine-naïve subjects who received placebo only. SAEs were monitored from the day of the first study vaccination through at least 6 months after the last study vaccination.

Among the smallpox vaccine-naïve subjects, SAEs were reported for 1.5% of JYNNEOS recipients and 1.1% of placebo recipients. Among the smallpox vaccine-experienced subjects enrolled in studies without a placebo comparator, SAEs were reported for 2.3% of JYNNEOS recipients. Across all studies, a causal relationship to JYNNEOS could not be excluded for 4 SAEs, all non-fatal, which included Crohn’s disease, sarcoidosis, extraocular muscle paresis and throat tightness.

Cardiac Adverse Events of Special Interest

Evaluation of cardiac adverse events of special interest (AESIs) included any cardiac signs or symptoms, ECG changes determined to be clinically significant, or troponin-I elevated above 2 times the upper limit of normal. In the 22 studies, subjects were monitored for cardiac-related signs or symptoms through at least 6 months after the last vaccination.

The numbers of JYNNEOS and placebo recipients, respectively, with troponin-I data were: baseline level (6,376 and 1,203); level two weeks after first dose (6,279 and 1,166); level two weeks after second dose (1,683 and 193); unscheduled visit, including for clinical evaluation of suspected cardiac adverse events (500 and 60).

Cardiac AESIs were reported to occur in 1.3% (95/7,093) of JYNNEOS recipients and 0.2% (3/1,206) of placebo recipients who were smallpox vaccine-naïve. Cardiac AESIs were reported to occur in 2.1% (16/766) of JYNNEOS recipients who were smallpox vaccine-experienced. The higher proportion of JYNNEOS recipients who experienced cardiac AESIs was driven by 28 cases of asymptomatic post-vaccination elevation of troponin-I in two studies: Study 5, which enrolled 482 HIV-infected subjects and 97 healthy subjects, and Study 6, which enrolled 350 subjects with atopic dermatitis and 282 healthy subjects. An additional 127 cases of asymptomatic post-vaccination elevation of troponin-I above the upper limit of normal but not above 2 times the upper limit of normal were documented in JYNNEOS recipients throughout the clinical development program, 124 of which occurred in Study 5 and Study 6. Proportions of subjects with troponin-I elevations were similar between healthy and HIV-infected subjects in Study 5 and between healthy and atopic dermatitis subjects in Study 6. A different troponin assay was used in these two studies compared to the other studies, and these two studies had no placebo controls. The clinical significance of these asymptomatic post-vaccination elevations of troponin-I is unknown.

Among the cardiac AESIs reported, 6 cases (0.08%) were considered to be causally related to JYNNEOS vaccination and included tachycardia, electrocardiogram T wave inversion, electrocardiogram abnormal, electrocardiogram ST segment elevation, electrocardiogram T wave abnormal, and palpitations.

None of the cardiac AESIs considered causally related to study vaccination were considered serious.

6.2 Postmarketing Experience

The following adverse reactions have been identified during postmarketing use of JYNNEOS. Because these reactions are reported voluntarily from a population of uncertain size, it is not always possible to reliably estimate their frequency or establish a causal relationship to vaccine exposure.

Cardiac Disorders: myocarditis, pericarditis

Immune System Disorders: hypersensitivity reactions, including angioedema, rash, and urticaria

Nervous System Disorders: dizziness, syncope

General disorders and administration site conditions: injection site warmth, injection site vesicles

8 USE IN SPECIFIC POPULATIONS

8.1 Pregnancy

Risk Summary

All pregnancies have a risk of birth defect, loss, or other adverse outcomes. In the US general population, the estimated background risk of major birth defects and miscarriage in clinically recognized pregnancies is 2% to 4% and 15% to 20%, respectively. Available human data on JYNNEOS administered to pregnant women are insufficient to inform vaccine-associated risks in pregnancy.

The effect of JYNNEOS on embryo-fetal and post-natal development was evaluated in four developmental toxicity studies conducted in female rats and rabbits. In two studies, rats were administered a single human dose of JYNNEOS (0.5 mL) once prior to mating and on one or two occasions during gestation. In the third study, rats were administered a single human dose of JYNNEOS (0.5 mL) on two occasions during gestation. In the fourth study, rabbits were administered a single human dose of JYNNEOS (0.5 mL) once prior to mating and on two occasions during gestation. These animal studies revealed no evidence of harm to the fetus [see Data].

Data

Animal Data

Developmental toxicity studies were conducted in female rats and rabbits. In one study, female rabbits were administered a single human dose of JYNNEOS (0.5 mL) by the subcutaneous route on three occasions: prior to mating, and on gestation days 0 and 14. Three studies were conducted in female rats administered a single human dose of JYNNEOS (0.5 mL) by the subcutaneous route on two or three occasions: prior to mating, and on gestation days 0 and 14; or prior to mating, and on gestation day 0; or on gestation days 0 and 6. No vaccine-related fetal malformations or variations and adverse effects on female fertility or pre-weaning development were reported in these studies.

8.2 Lactation

Risk Summary

It is not known whether JYNNEOS is excreted in human milk. Data are not available to assess the effects of JYNNEOS in the breastfed infant or on milk production/excretion.

The development and health benefits of breastfeeding should be considered along with the mother’s clinical need for JYNNEOS and any potential adverse effects on the breastfed child from JYNNEOS or from the underlying maternal condition. For preventive vaccines, the underlying condition is susceptibility to disease prevented by the vaccine.

8.4 Pediatric Use

Safety and effectiveness of JYNNEOS have not been established in individuals less than 18 years of age.

8.5 Geriatric Use

Forty-two smallpox vaccine-experienced adults 65 to 80 years of age received at least one dose of JYNNEOS (Study 4).

Clinical studies of JYNNEOS did not include sufficient numbers of subjects aged 65 and over to determine whether they respond differently from younger subjects.

11 DESCRIPTION

When thawed, JYNNEOS (Smallpox and Monkeypox Vaccine, Live, Non replicating) is a milky, light yellow to pale white colored suspension for subcutaneous injection.

JYNNEOS is a live vaccine produced from the strain Modified Vaccinia Ankara-Bavarian Nordic (MVA-BN), an attenuated, non-replicating orthopoxvirus. MVA-BN is grown in primary Chicken Embryo Fibroblast (CEF) cells suspended in a serum-free medium containing no material of direct animal origin, harvested from the CEF cells, purified and concentrated by several Tangential Flow Filtration (TFF) steps including benzonase digestion. Each 0.5 mL dose is formulated to contain 0.5 x 10^8 to 3.95 x 10^8 infectious units of MVA-BN live virus in 10 mM Tris (tromethamine), 140 mM sodium chloride at pH 7.7. Each 0.5 mL dose may contain residual amounts of host-cell DNA (≤ 20 mcg), protein (≤ 500 mcg), benzonase (≤ 0.0025 mcg), gentamicin (≤ 0.400 mcg) and ciprofloxacin (≤ 0.005 mcg).

JYNNEOS is a sterile vaccine formulated without preservatives. The vial stoppers are not made with natural rubber latex.

12 CLINICAL PHARMACOLOGY

12.1 Mechanism of Action

JYNNEOS is an attenuated, live, non-replicating smallpox and monkeypox vaccine that elicits humoral and cellular immune responses to orthopoxviruses. Vaccinia neutralizing antibody responses in humans were evaluated to establish the effectiveness of JYNNEOS for prevention of smallpox and monkeypox.

13 NONCLINICAL TOXICOLOGY

13.1 Carcinogenesis, Mutagenesis, Impairment of Fertility

JYNNEOS has not been evaluated for carcinogenic or mutagenic potential, or for impairment of male fertility in animals. Developmental toxicity studies conducted in rats and rabbits vaccinated with JYNNEOS revealed no evidence of impaired female fertility [see Use in Specific Populations (8.1)].

13.2 Animal Toxicology and/or Pharmacology

The efficacy of JYNNEOS to protect cynomolgus macaques (Macaca fascicularis) against a monkeypox virus (MPXV) challenge was evaluated in several studies. Animals were administered Tris-Buffered Saline (placebo) or JYNNEOS (1 x 10^8 TCID50) subcutaneously on day 0 and day 28. On day 63, animals were challenged with MPXV delivered by aerosol (3 x 10^5 pfu), intravenous (5 x 10^7 pfu) or intratracheal (5 x 10^6 pfu) route. Across all studies, 80-100% of JYNNEOS-vaccinated animals survived compared to 0-40% of control animals.

14 CLINICAL STUDIES

14.1 Vaccine Effectiveness

Vaccine effectiveness against smallpox was inferred by comparing the immunogenicity of JYNNEOS to a licensed smallpox vaccine (ACAM2000) based on a Plaque Reduction Neutralization Test (PRNT) using the Western Reserve strain of vaccinia virus and was supported by efficacy data from animal challenge studies. [see Nonclinical Toxicology (13.2)]

Vaccine effectiveness against monkeypox was inferred from the immunogenicity of JYNNEOS in a clinical study and from efficacy data from animal challenge studies. [see Nonclinical Toxicology (13.2)]

14.2 Immunogenicity

Study 7 [7] (N=433) was a randomized, open-label study conducted at US military facilities in South Korea to compare the immunogenicity of JYNNEOS to ACAM2000 in healthy smallpox vaccine-naïve adults 18 through 42 years of age. Subjects were randomized to receive either two doses of JYNNEOS (N=220) administered 28 days apart or one dose of ACAM2000 (N=213). In the total study population, the mean age was 24 years and 23 years in subjects receiving JYNNEOS and ACAM2000, respectively; 82.3% and 86.4% of the subjects were men; 57.3% and 63.8% were white/Caucasian, 21.8% and 18.8% black/African American, 6.4% and 5.6% Asian, 3.6% and 2.8% American Indian/Alaska Native, 2.3% and 1.4% Native Hawaiian/Other Pacific, 8.6% and 7.5% other racial groups, and 24.5% and 18.8% of Hispanic/Latino ethnicity (JYNNEOS and ACAM2000, respectively).

The primary immunogenicity endpoint was geometric mean titer (GMT) of vaccinia neutralizing antibodies assessed by PRNT at “peak visits” defined as two weeks after the second dose of JYNNEOS and four weeks after the single dose of ACAM2000. Analyses of antibody responses were performed in the per-protocol immunogenicity (PPI) population, consisting of individuals who received all vaccinations and completed all visits up until the peak visit without major protocol violations pertaining to immunogenicity assessments. Table 2 presents the pre-vaccination and “peak visit” PRNT GMTs from Study 7.

Table 2: Comparison of Vaccinia-Neutralizing Antibody Responses Following Vaccination with JYNNEOS or ACAM2000 in Healthy Smallpox Vaccine-Naïve Adults 18 through 42 Years of Age, Study 7x, Per Protocol Set for Immunogenicityy
Time Point | JYNNEOSa (N=185) GMTb [95% CI] | ACAM2000a (N=186) GMTb [95% CI]
Pre-Vaccination | 10.1 [9.9, 10.2] | 10.0 [10.0, 10.0]
Post-Vaccination “Peak Visit”y | 152.8c [133.3, 175.0] | 84.4c [73.4, 97.0]
x NCT01913353
y Per Protocol Set for Immunogenicity included subjects who received all vaccinations, completed all visits up until the specified “peak visits” (two weeks after the second dose of JYNNEOS or 4 weeks after the single dose of ACAM2000) without major protocol violations pertaining to immunogenicity assessments.
a JYNNEOS was administered as a series of two doses given 28 days apart, and ACAM2000 was administered as a single dose.
b GMT of vaccinia-neutralizing antibody titers assessed by plaque reduction neutralization test (PRNT) using the Western Reserve vaccinia strain. Values below the assay lower limit of quantitation (LLOQ) of 20 were imputed to a titer of 10; the proportions of subjects with pre-vaccination titers less than the assay lower limit of detection were 98.9% among subjects randomized to JYNNEOS and 97.8% among subjects randomized to ACAM2000, respectively.
c Non-inferiority of the “peak visit” PRNT GMT for JYNNEOS compared to ACAM2000 was demonstrated as the lower bound of the 1-sided 97.5% CI for the GMT ratio (JYNNEOS/ACAM2000) was > 0.5.
N: Number of subjects in the specified treatment group; GMT: Geometric Mean Titer; 95% CI: 95% confidence interval, lower limit and upper limit.

PRNT GMTs were also evaluated at pre-specified time points post-vaccination and prior to the “peak visits”. The PRNT GMTs at two and four weeks after the first dose of JYNNEOS (prior to the second dose), were 23.4 (95% CI: 20.5, 26.7) and 23.5 (95% CI: 20.6, 26.9), respectively. The PRNT GMT at two weeks after the single dose of ACAM2000 was 23.7 (95% CI: 20.9, 26.8).

15 REFERENCES

1. Study 1: NCT01144637
2. Study 2: NCT00316524
3. Study 3: NCT00686582
4. Study 4: NCT00857493
5. Study 5: NCT00316589
6. Study 6: NCT00316602
7. Study 7: NCT01913353

16 HOW SUPPLIED/STORAGE AND HANDLING

16.1 How Supplied

• Package of 10 single-dose vials

(Package NDC number: 50632-001-03; Vial NDC number: 50632-001-01)

• Package of 20 single-dose vials

(Package NDC number: 50632-001-02; Vial NDC number: 50632-001-01)

16.2 Storage Conditions

Keep frozen at -25°C to -15°C (-13°F to +5°F).
Store in the original package to protect from light.
Do not re-freeze a vial once it has been thawed.
Once thawed, the vaccine may be kept at +2°C to +8°C (+36°F to +46°F) for 4 weeks.
Do not use the vaccine after the expiration date shown on the vial label.

17 PATIENT COUNSELING INFORMATION

•Inform vaccine recipient of the potential benefits and risks of vaccination with JYNNEOS.

•Inform vaccine recipient of the importance of completing the two dose vaccination series.

•Advise vaccine recipient to report any adverse events to their healthcare provider or to the Vaccine Adverse Event Reporting System at 1-800-822-7967 and www.vaers.hhs.gov.

Manufactured for:
Bavarian Nordic A/S
Philip Heymans Alle 3
2900 Hellerup
Denmark

PRINCIPAL DISPLAY PANEL - Carton Label - 20 vials

NDC 50632-001-02

Smallpox and Monkeypox Rx only
Vaccine, Live, Non-replicating

JYNNEOS®

Suspension for subcutaneous injection

Contains 20 single-dose 0.5 mL vials

BAVARIAN NORDIC

PRINCIPAL DISPLAY PANEL - Carton Label - 10 vials

NDC 50632-001-03

Smallpox and Monkeypox Rx only
Vaccine, Live, Non-replicating

JYNNEOS®

Suspension for subcutaneous injection

Contains 10 single-dose 0.5 mL vials

BAVARIAN NORDIC

PRINCIPAL DISPLAY PANEL - Vial Label

Smallpox and Monkeypox
Vaccine, Live, Non-replicating

JYNNEOS®

Single-dose: 0.5 mL

Bavarian Nordic A/S

U.S. Govt. Lic. No. 2096

LOT: XXXXXXXX